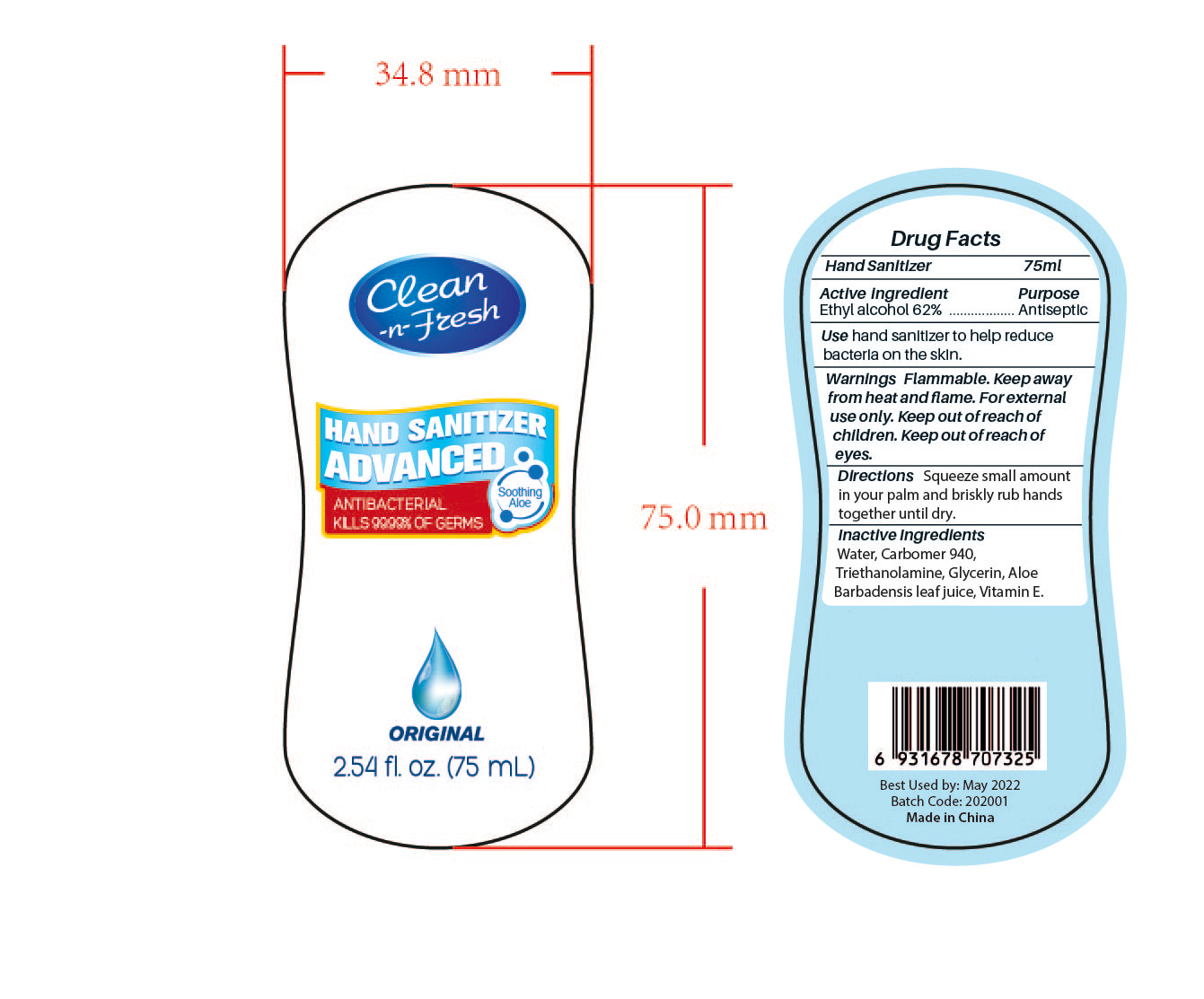 DRUG LABEL: HAND SANITIZER
NDC: 47993-235 | Form: GEL
Manufacturer: NINGBO JIANGBEI OCEAN STAR TRADING CO.,LTD
Category: otc | Type: HUMAN OTC DRUG LABEL
Date: 20201104

ACTIVE INGREDIENTS: ALCOHOL 62 g/112 mL
INACTIVE INGREDIENTS: CARBOMER 940; WATER; GLYCERIN; TRIETHANOLAMINE BENZOATE; ALOE VERA LEAF; TOCOPHEROL

47993-235

Active ingredients

Ethyl Alcohol 62%

PURPOSE

Antiseptic

Warnings:

Flammable.Keep away from fire or flame.For external use only.Keep out of reach of children.Keep out of reach of eyes.

Uses：

Hand sanitizer to help reduce bacteria on the skin.

Directions:

Squeeze small amount in your palm and briskly rub hands together until dry.

Keep out of reach of children.

Inactive Ingredients:

Water,Carbomer 940,Triethanolamine,Glycerin,Aloe Barbadensis leaf juice,Vitamin E